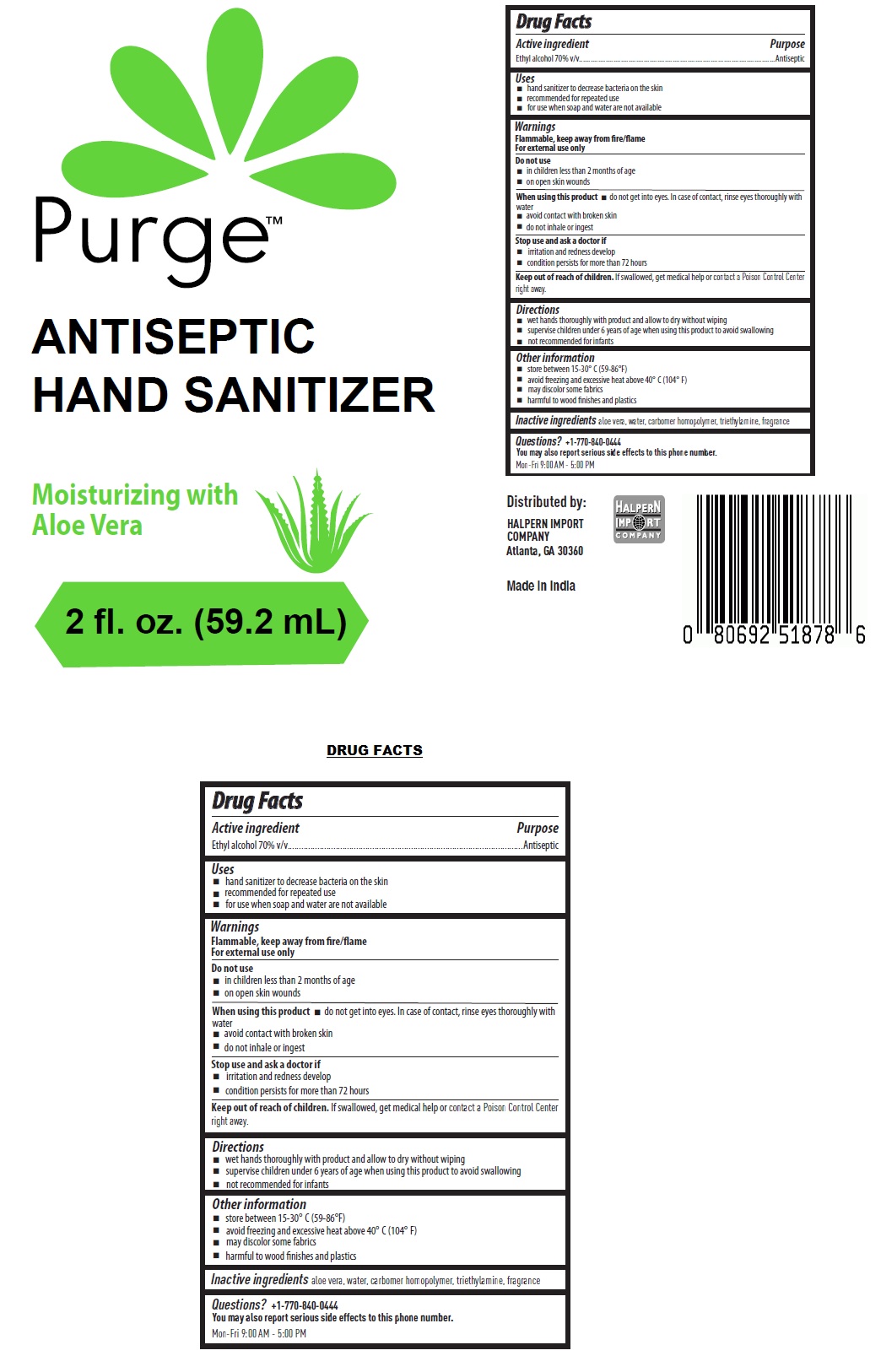 DRUG LABEL: Purge Hand Sanitizer
NDC: 79698-001 | Form: GEL
Manufacturer: OHAD PHARMACEUTICALS PRIVATE LIMITED
Category: otc | Type: HUMAN OTC DRUG LABEL
Date: 20200917

ACTIVE INGREDIENTS: ALCOHOL 70 mL/100 mL
INACTIVE INGREDIENTS: ALOE VERA LEAF; WATER; CARBOMER HOMOPOLYMER, UNSPECIFIED TYPE; TRIETHYLAMINE

Purge™ ANTISEPTIC HAND SANITIZER

Active ingredient

Ethyl alcohol 70% v/v

Purpose

Antiseptic

Uses

• hand sanitizer to decrease bacteria on the skin

• recommended for repeated use

• for use when soap and water are not available

Warnings

Flammable, keep away from fire/flame
For external use only

Do not use

• in children less than 2 months of age

• on open skin wounds

When using this product • do not get into eyes. In case of contact, rinse eyes thoroughly with water

• avoid contact with broken skin

• do not inhale or ingest

Stop use and ask a doctor if

• irritation and redness develop

• condition persists for more than 72 hours

Keep out of reach of children. If swallowed, get medical help or contact a Poison Control Center
right away.

Directions

• wet hands thoroughly with product and allow to dry without wiping

• supervise children under 6 years of age when using this product to avoid swallowing

• not recommended for infants

Other information

• store between 15-30° C (59-86°F)

• avoid freezing and excessive heat above 40° C (104° F)

• may discolor some fabrics

• harmful to wood finishes and plastics

Inactive ingredients

aloe vera, water, carbomer homopolymer, triethylamine, fragrance

Questions?

+1-770-840-0444

You may also report serious side effects to this phone number.

Mon-Fri 9:00 AM - 5:00 PM

Moisturizing with Aloe Vera

Distributed by:

HALPERN IMPORT COMPANY

Atlanta, GA 30360

Made in India